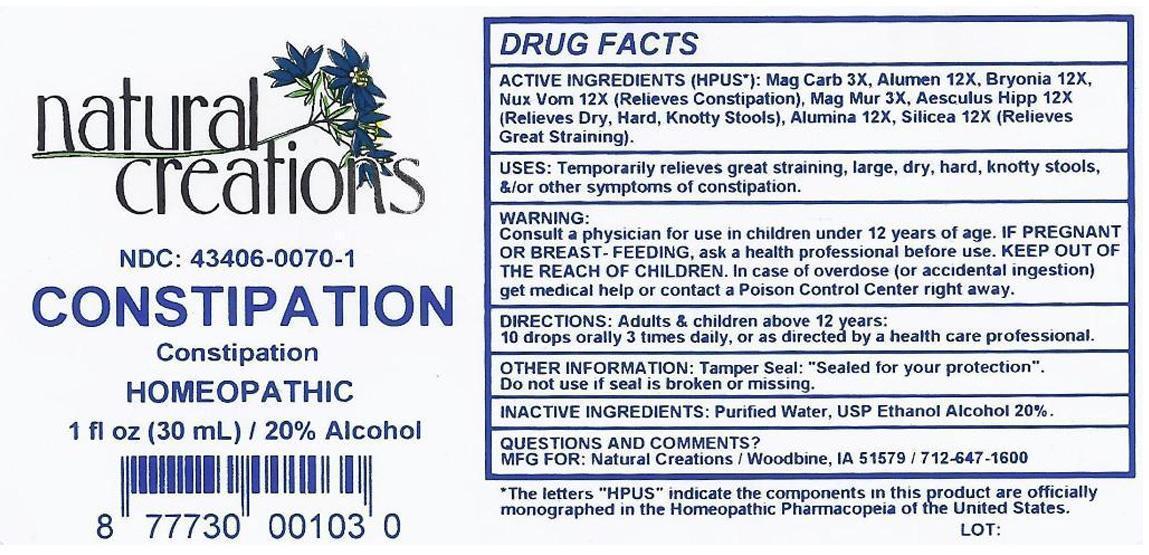 DRUG LABEL: CONSTIPATION
NDC: 43406-0070 | Form: LIQUID
Manufacturer: Natural Creations, Inc.
Category: homeopathic | Type: HUMAN OTC DRUG LABEL
Date: 20130121

ACTIVE INGREDIENTS: MAGNESIUM CARBONATE 3 [hp_X]/1 mL; MAGNESIUM CHLORIDE 3 [hp_X]/1 mL; AESCULUS HIPPOCASTANUM FLOWER 12 [hp_X]/1 mL; POTASSIUM ALUM 12 [hp_X]/1 mL; ALUMINUM OXIDE 12 [hp_X]/1 mL; BRYONIA ALBA ROOT 12 [hp_X]/1 mL; STRYCHNOS NUX-VOMICA SEED 12 [hp_X]/1 mL; SILICON DIOXIDE 12 [hp_X]/1 mL
INACTIVE INGREDIENTS: WATER; ALCOHOL

CONSTIPATION

ACTIVE INGREDIENT

ACTIVE INGREDIENTS (HPUS*): Magnesium Carbonicum 3X, Magnesium Muriaticum 3X, Aesculus Hippocastanum 12X, Alumen 12X, Alumina 12X, Bryonia Alba 12X, Nux Vomica 12X, Silicea 12X

PURPOSE

USES: Temporarily relieves great straining, large, dry, hard, knotty stools, &/or other symptoms of constipation.

KEEP OUT OF REACH OF CHILDREN

KEEP OUT OF THE REACH OF CHILDREN. In case of overdose (or accidental ingestion) get medical help or contact a Poison Control Center.

INDICATIONS AND USAGE

USES: Temporarily relieves great straining, large, dry, hard, knotty stools, &/or other symptoms of constipation.

WARNING:

Consult a physician for use in children under 12 years of age. IF PREGNANT OR BREAST-FEEDING, ask a health professional before use. KEEP OUT OF THE REACH OF CHILDREN. In case of overdose (or accidental ingestion) get medical help or contact a Poison Control Center right away.

DOSAGE AND ADMINISTRATION

DIRECTIONS: Adults & children above 12 years: 10 drops orally 3 times daily, or as directed by a health care professional.

INACTIVE INGREDIENTS: Purified Water, USP Ethanol Alcohol 20%

PACKAGE LABEL

NDC: 43406-0070-1

CONSTIPATION

Constipation

HOMEOPATHIC

1 fl oz (30 mL) / 20% Alcohol

UPC: 877730001030